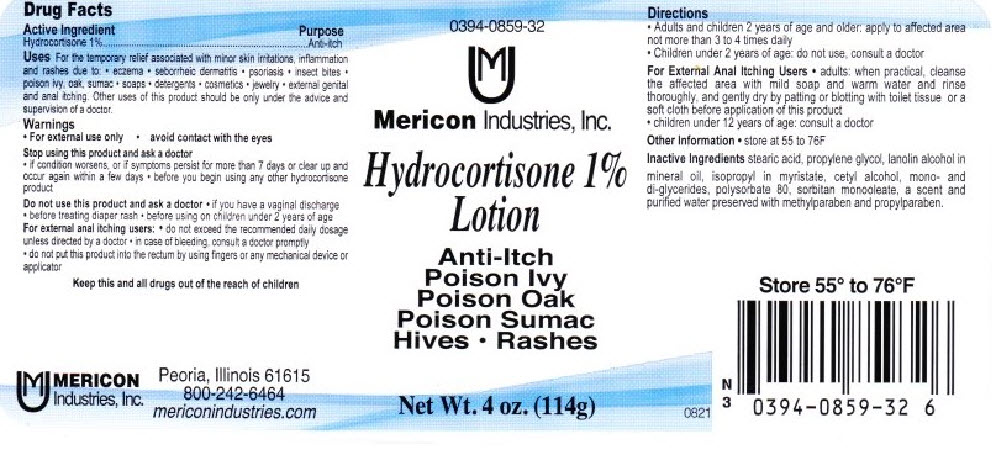 DRUG LABEL: Hydrocortisone
NDC: 0394-0859 | Form: LOTION
Manufacturer: Mericon Industries
Category: otc | Type: HUMAN OTC DRUG LABEL
Date: 20241227

ACTIVE INGREDIENTS: Hydrocortisone 1.14 g/114 g
INACTIVE INGREDIENTS: stearic acid; propylene glycol; lanolin alcohols; mineral oil; MYRISTIC ACID; cetyl alcohol; polysorbate 80; sorbitan monooleate; water; methylparaben; propylparaben

Hydrocortisone

Drug Facts

Active Ingredient

Hydrocortisone 1%

Purpose

Anti-itch

Uses

For the temporary relief associated with minor skin irritations, inflammation and rashes due to:

- eczema
- seborrheic dermatitis
- psoriasis
- insect bites
- poison ivy, oak, sumac
- soaps
- detergents
- cosmetics
- jewelry
- external genital and anal itching.

Other uses of this product should be only under the advice and supervision of a doctor.

Warnings

- For external use only
- avoid contact with the eyes

Stop using this product and ask a doctor

- if condition worsens, or if symptoms persist for more than 7 days or clear up and occur again within a few days
- before you begin using any other hydrocortisone product

Do not use this product and ask a doctor

- if you have a vaginal discharge
- before treating diaper rash
- before using on children under 2 years of age

For external anal itching users

- do not exceed the recommended daily dosage unless directed by a doctor
- in case of bleeding, consult a doctor promptly
- do not put this product into the rectum by using fingers or any mechanical device or applicator

KEEP OUT OF REACH OF CHILDREN

Keep this and all drugs out of the reach of children

Directions

- Adults and children 2 years of age and older: apply to affected area not more than 3 to 4 times daily
- Children under 2 years of age: do not use, consult a doctor

For External Anal Itching Users

- adults: when practical, cleanse the affected area with mild soap and warm water and rinse thoroughly, and gently dry by patting or blotting with toilet tissue or a soft cloth before application of this product
- children under 12 years of age: consult a doctor

Other Information

- store at 55 to 76F

Inactive Ingredients

stearic acid, propylene glycol, lanolin alcohol in mineral oil, isopropyl in myristate, cetyl alcohol, mono- and di-glycerides, polysorbate 80, sorbitan monooleate, a scent and purified water preserved with methylparaben and propylparaben.

PRINCIPAL DISPLAY PANEL - 114 g Bottle Label

0394-0859-32

Mericon Industries, Inc.

Hydrocortisone 1%
Lotion

Anti-Itch
Poison Ivy
Poison Oak
Poison Sumac
Hives • Rashes

Net Wt. 4 oz. (114g)